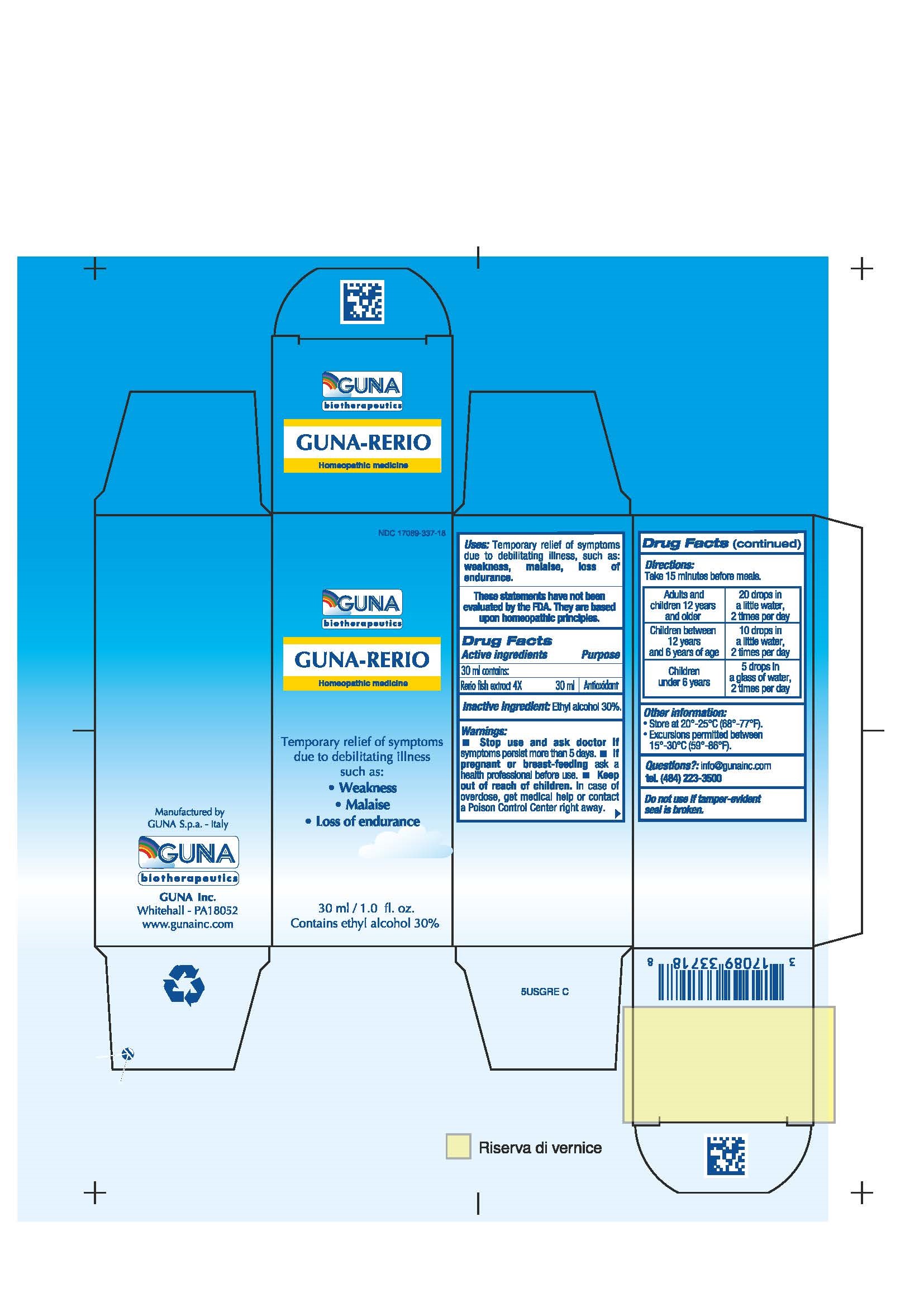 DRUG LABEL: GUNA-RERIO
NDC: 17089-337 | Form: SOLUTION/ DROPS
Manufacturer: Guna spa
Category: homeopathic | Type: HUMAN OTC DRUG LABEL
Date: 20181221

ACTIVE INGREDIENTS: DANIO RERIO EGG 4 [hp_X]/30 mL
INACTIVE INGREDIENTS: ALCOHOL 9 mL/30 mL

GUNA-RERIO

ACTIVE INGREDIENTS/PURPOSE

Rerio fish extract 4x Antioxidant

USES

Temporary relief of symptoms due to debilitating illness such as:

- Weakness
- Malaise
- Loss of endurance

WARNINGS

Stop use and ask doctor if symptoms persist more than 5 days.
If pregnant or breast-feeding ask a health professional before use.
Keep out of reach of children. In case of overdose, get medical help or contact a Poison Control Center right away.
Contains ethyl alcohol 30%

PREGNANCY

If pregnant or breast-feeding ask a doctor before use

WARNINGS

Keep out of reach of children

DIRECTIONS

Take 15 minutes before meals
Adults and children 12 years and older 20 drops in a little water, 2 times per day
Children between 12 years and 6 years of age 10 drops in a little water, 2 times per day
Children under 6 years 5 drops in a glass of water, 2 times per day

QUESTIONS

Questions?: info@gunainc.com, tel. (484) 223-3500

INDICATIONS AND USAGE

Take 15 minutes before meals

Inactive ingredient: Ethyl alcohol 30%.